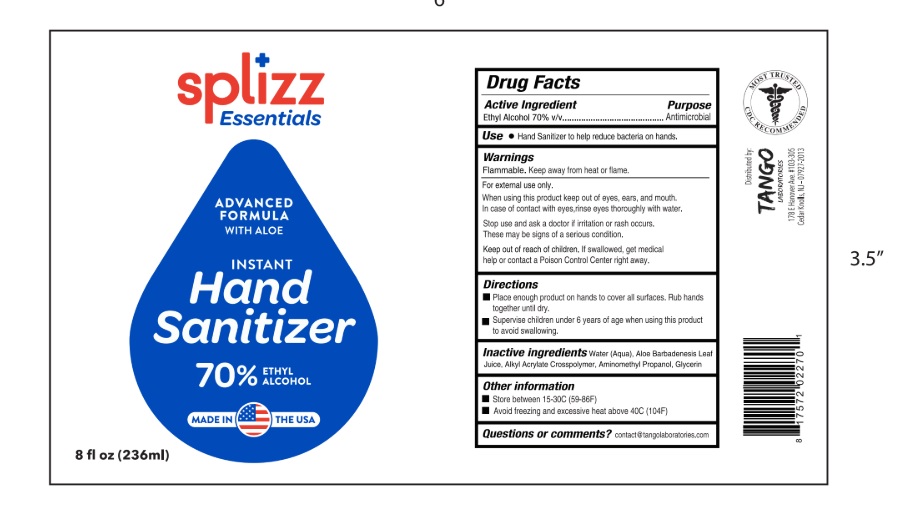 DRUG LABEL: Splizz Essentials
NDC: 77356-717 | Form: GEL
Manufacturer: Adonis, LLC.
Category: otc | Type: HUMAN OTC DRUG LABEL
Date: 20200714

ACTIVE INGREDIENTS: ALCOHOL 70 mL/100 mL
INACTIVE INGREDIENTS: WATER; ALOE VERA LEAF; BUTYL ACRYLATE/METHYL METHACRYLATE/METHACRYLIC ACID COPOLYMER (18000 MW); AMINOMETHYLPROPANOL; GLYCERIN

Splizz Essentials- Gel Hand Sanitizer

Active Ingredient(s)

Ethyl Alcohol 70% v/v. .......... Antimicrobial

Purpose

Antimicrobial, Hand Sanitizer

Use

Hand Sanitizer to help reduce bacteria on hands.

Warnings

For external use only. Flammable. Keep away from heat or flame

Do not use

- in children less than 2 months of age
- on open skin wounds

When using this product avoid contact with eyes. If contact occurs, rinse rinse eyes thoroughly with water.

Stop use and ask a doctor if irritation or redness devleops and lasts.

Keep out of reach of children. If swallowed, get medical help or contact a Poison Control Center immediately.

Directions

- Place enough product on hands to cover all surfaces. Rub hands together until dry.
- Supervise children under 6 years of age when using this product to avoid swallowing.

Other information

- Store between 15-30C(59-86F)
- Avoid freezing and excessive heat above (104F)

Inactive ingredients

glycerin, purified water ,Aloe Barbadensis, Alkyl Acrylates Crosspolymer ,Aminomethyl Propanol